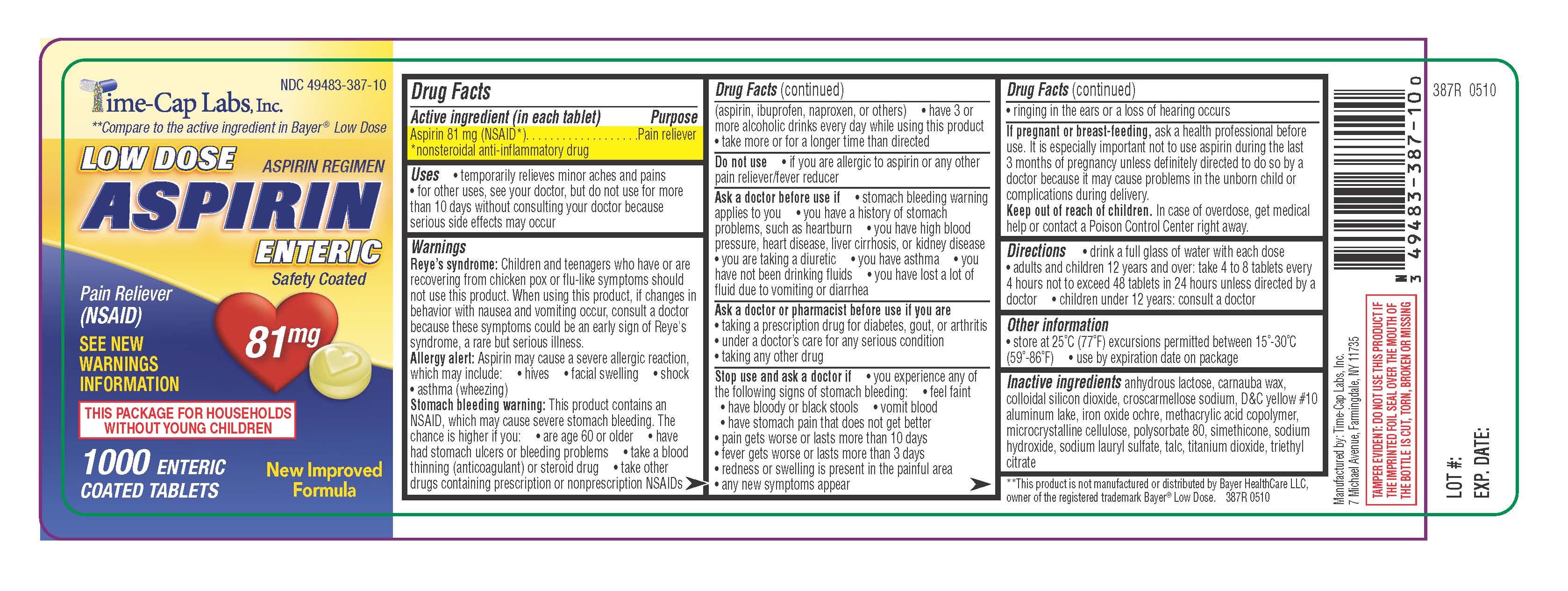 DRUG LABEL: aspirin
NDC: 49483-387 | Form: TABLET, COATED
Manufacturer: Time-Cap Labs, Inc
Category: otc | Type: HUMAN OTC DRUG LABEL
Date: 20181217

ACTIVE INGREDIENTS: ASPIRIN 81 mg/1 1
INACTIVE INGREDIENTS: ANHYDROUS LACTOSE; CARNAUBA WAX; SILICON DIOXIDE; CROSCARMELLOSE SODIUM; D&C YELLOW NO. 10; IRON; METHACRYLIC ACID - ETHYL ACRYLATE COPOLYMER (1:1) TYPE A; CELLULOSE, MICROCRYSTALLINE; DIMETHICONE; POLYSORBATE 80; SODIUM HYDROXIDE; SODIUM LAURYL SULFATE; TALC; TITANIUM DIOXIDE; TRIETHYL CITRATE

387R ASA

Active Ingredient in Each tablet

Aspirin 81 mg (NSAID) Non-steroidal anti-inflammatory drug

Ask a doctor before use if: stomach bleeding warning applies to you, you have a history of stomach problems, such as heartburn, you have high blood pressure, heart disease, liver cirrhosis, or kidney disease; you are taking a diuretic, you have asthma, you have not been drinking fluids, you have lost a lot of fluid due to vomiting or diarrhea

INDICATIONS AND USAGE

Uses: temporarily relieves minor aches and pains: for other uses, see your doctor, but do not use for more than 10 days without consulting your doctor because serious side effects may occur.

WARNINGS

Reye's syndrome: Children and teenagers who have or are recovering from chicken pox or flu-like symptoms should not use this product. When using this product, if changes in behavior with nausea and vomiting occur, consult a doctor because these symptoms could be an early sign of Reye's syndrome, a rare but serious illness

Allergy alert: Aspirin may cause a severe allergic reaction which may include: hives, facial swelling, shock, asthma(wheezing

Stomach bleeding warning: This product contains an NSAID which may cause severe stomach bleeding. The chance is higher if you: are age 60 or older, have had stomach ulcers or bleeding problems, take a blood thinning (anticoagulant) or steroid drug, take other drugs containing prescription or non prescription NSAIDs (aspirin, ibuprofen, naproxen, or others), have 3 or more alcoholic drinks every day while using this product, take more or for a longer time than directed.

Ask a doctor or pharmacist before use if you are taking a prescription drug for diabetes, gout, or arthritis; under a doctor's care for any serious condition; taking any other drug

Do not use if you are allergic to aspirin or any other pain reliever/fever reducer

Stop use and ask a doctor if: you experience any of the following signs of stomach bleeding: feel faint, have bloody or black stools, vomit blood, have stomach pain that does not get better, pain gets worse or lasts more than 10 days, fever gets worse or lasts more than 3 days, redness or swelling is present in the painful area, any new symptoms appear

PREGNANCY OR BREAST FEEDING

If pregnant or breast-feeding, ask a health profession before use. It is especially important not to use aspirin during the last 3 months of pregnancy unless definitely directed to do so by a doctor because it may cause problems in the unborn child or complications during delivery.

KEEP OUT OF REACH OF CHILDREN

eep out of the reach of children. In case of overdose, get medical help or contact a Poison Control Center right away.

K

DOSAGE AND ADMINISTRATION

Directions: drink a full glass of water with each dose; adults and children 12 years and over: take 4 to 8 tablets every 4 hours not to exceed 48 tablets in 24 hours unless directed by a doctor

Children under 12 years - consult a doctor

INACTIVE INGREDIENT

Inactive ingredients: anhydrous lactose, carnauba wax, colloidal silicon dioxide, croscarmellose sodium, D-C yellow #10 aluminum lake, iron oxide ochre, methacrylic acid copolymer, microcrystalline cellulose, Polysorbate 80, simethicone, sodium hydroxide, sodium lauryl sulfate, talc, titanium dioxide

PURPOSE

Uses - temporarily relieves minor aches and pains for other uses, see your doctor, but do not use for more than 10 days without consulting your doctor because serious side effects may occur

PACKAGE LABEL

Enter section text here